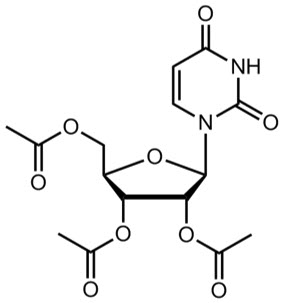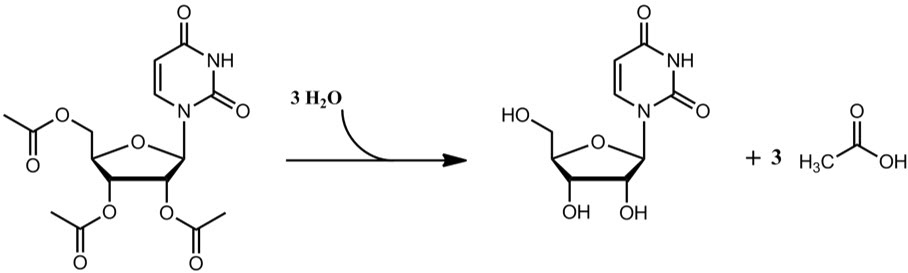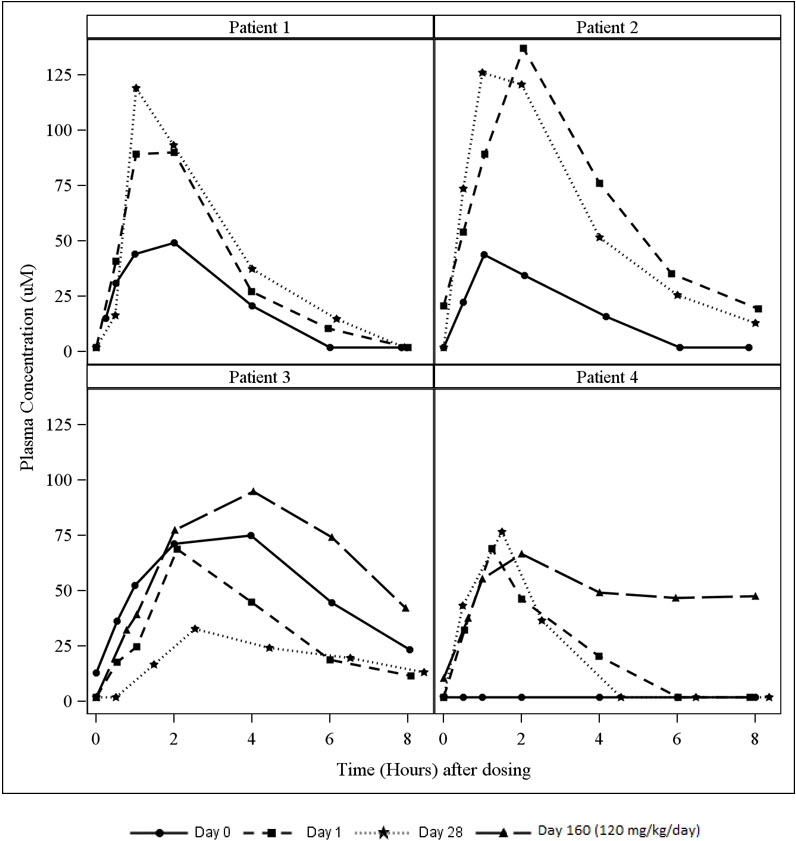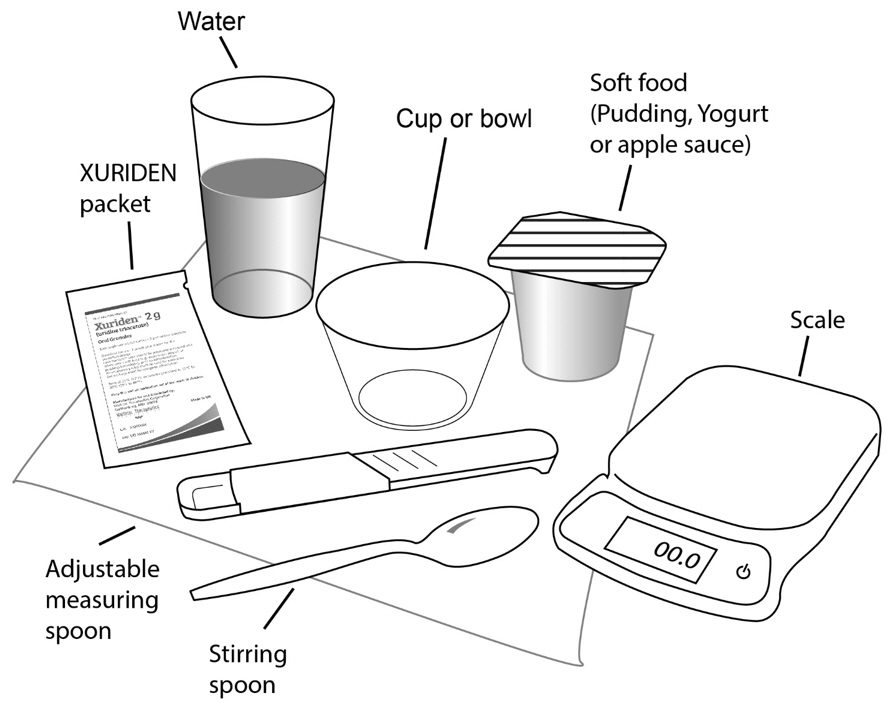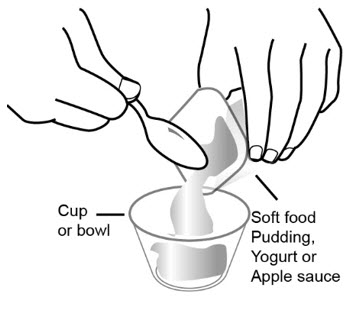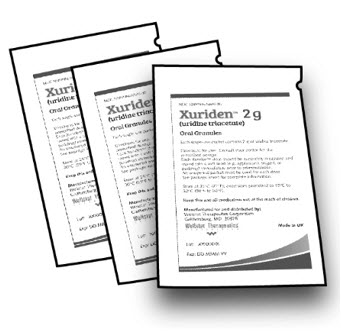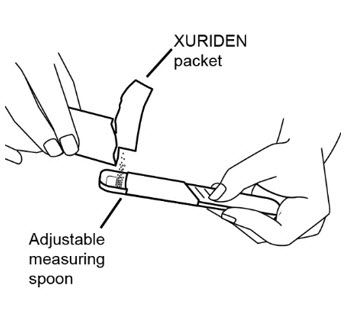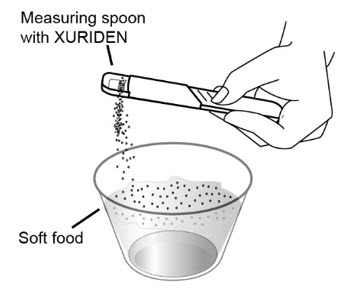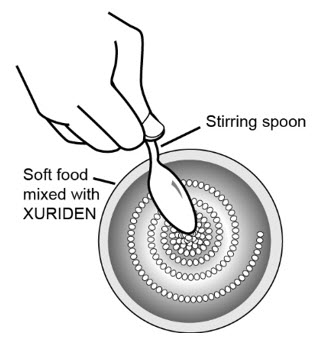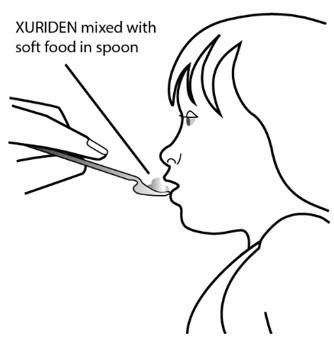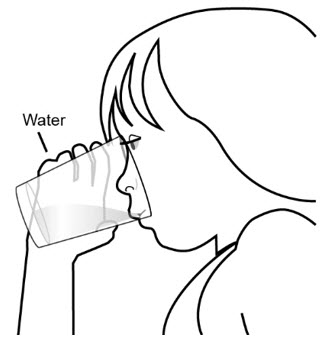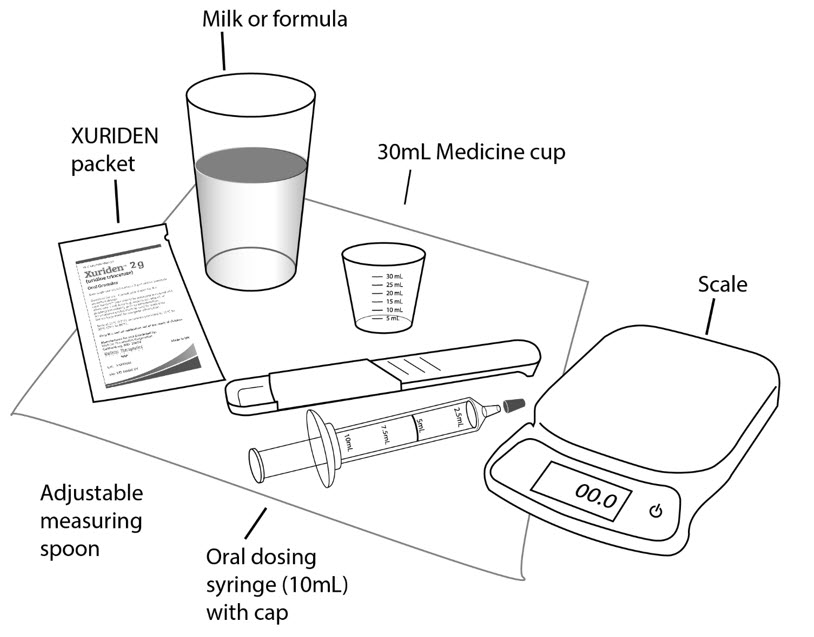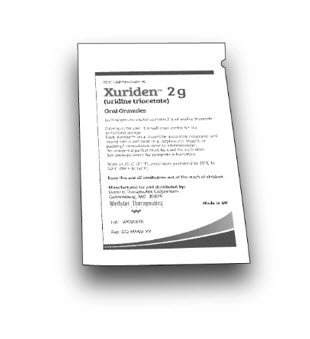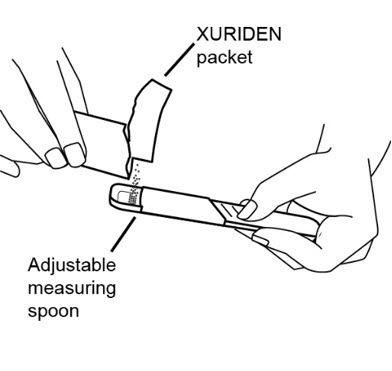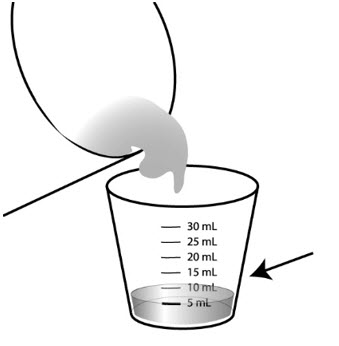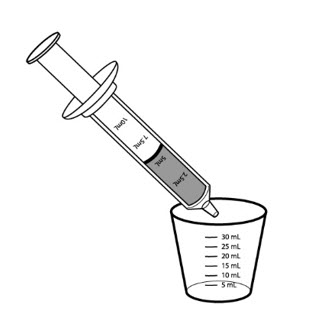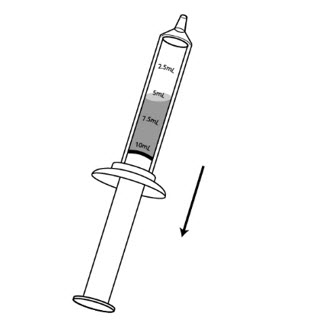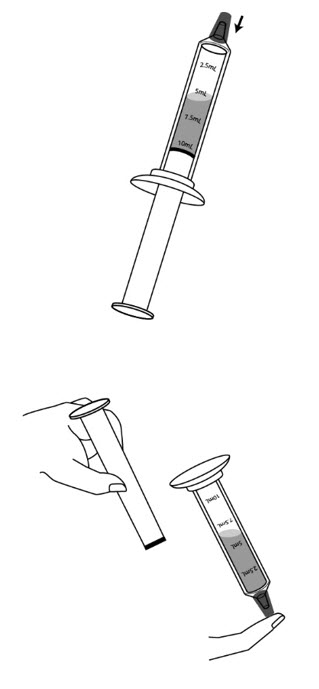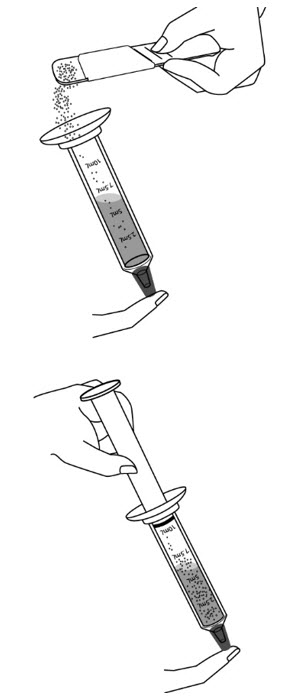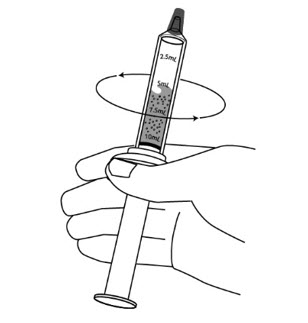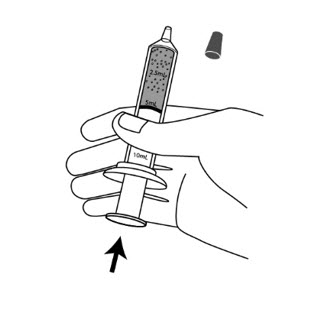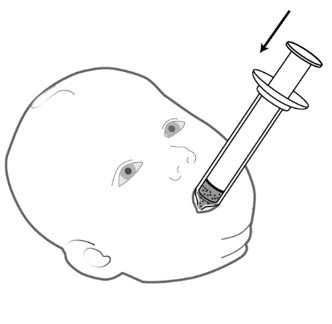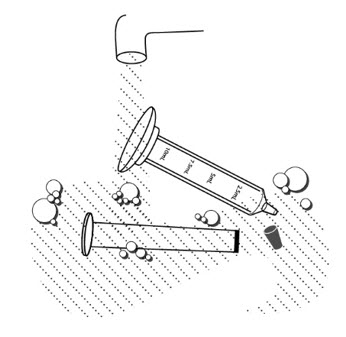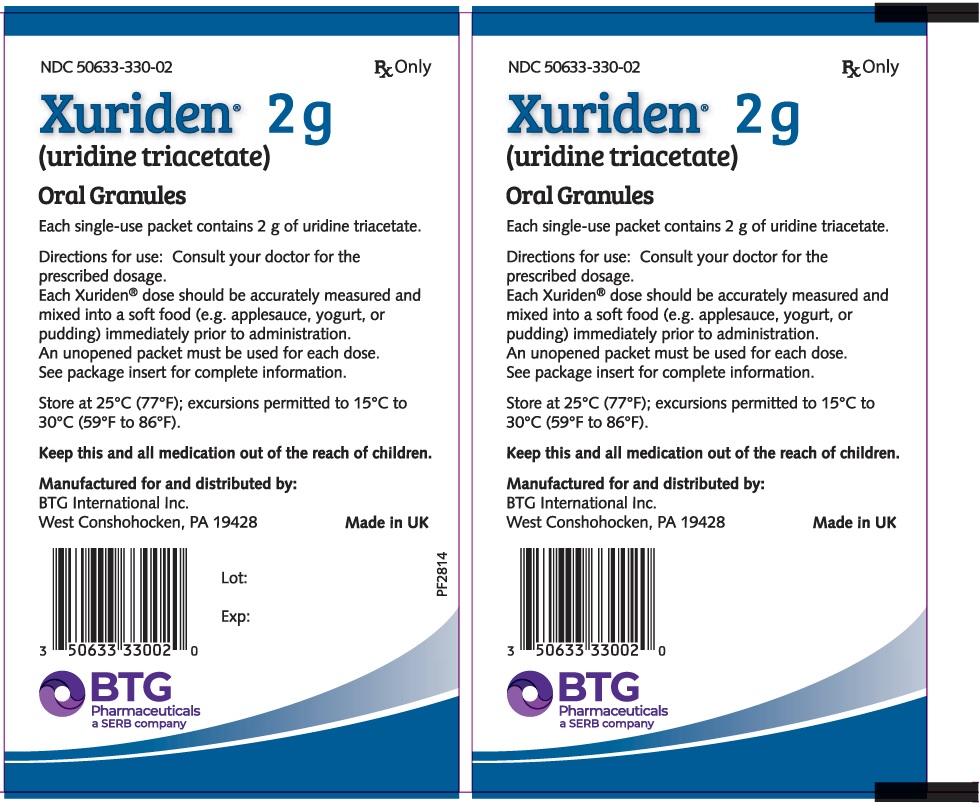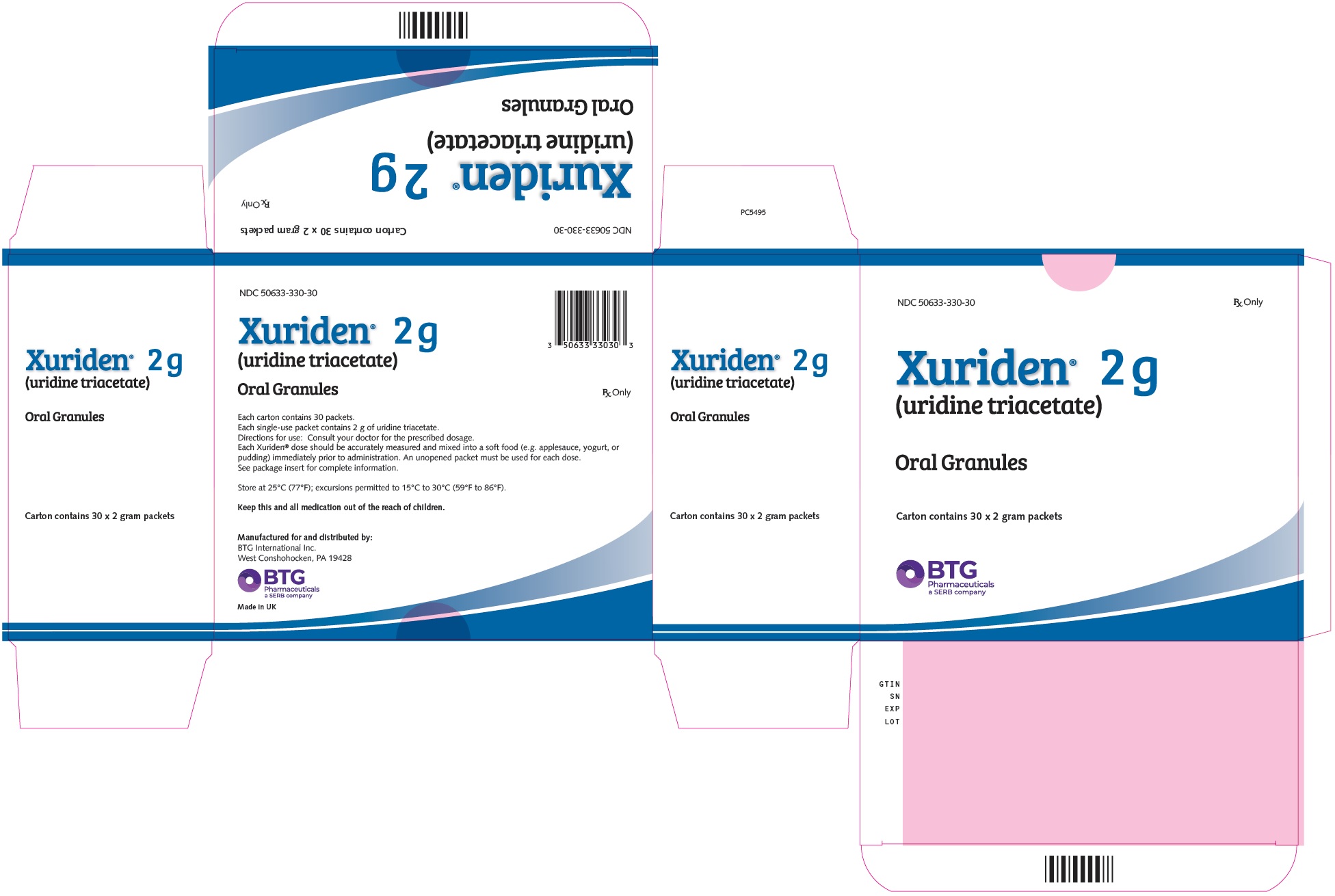 DRUG LABEL: XURIDEN
NDC: 50633-330 | Form: GRANULE
Manufacturer: BTG International Inc
Category: prescription | Type: HUMAN PRESCRIPTION DRUG LABEL
Date: 20250218

ACTIVE INGREDIENTS: URIDINE TRIACETATE 951 mg/1 g
INACTIVE INGREDIENTS: ORANGE JUICE; HYPROMELLOSE, UNSPECIFIED; POLYETHYLENE GLYCOL, UNSPECIFIED; ETHYLCELLULOSE, UNSPECIFIED

HIGHLIGHTS OF PRESCRIBING INFORMATION

These highlights do not include all the information needed to use XURIDEN safely and effectively. See full prescribing information for XURIDEN.
XURIDEN® (uridine triacetate) oral granules
Initial U.S. Approval: 2015

1 INDICATIONS AND USAGE

XURIDEN is a pyrimidine analog for uridine replacement indicated in adult and pediatric patients for the treatment of hereditary orotic aciduria. (1)

2 DOSAGE AND ADMINISTRATION

Recommended Dosage (2.1):

- The starting dosage is 60 mg/kg once daily; the dose may be increased to120 mg/kg (not to exceed 8 grams) once daily for insufficient efficacy.
- See the full prescribing information for 60 mg/kg and 120 mg/kg weight-based dosing tables.

Preparation and Administration (2.2)

- Measure the dose using either a scale accurate to at least 0.1 gram, or a graduated teaspoon, accurate to the fraction of the dose to be administered.
- Administer the dose with food (applesauce, pudding or yogurt) or in milk or infant formula. See full prescribing information for preparation and administration instructions.

3 DOSAGE FORMS AND STRENGTHS

Oral granules: 2 gram packets. (3)

4 CONTRAINDICATIONS

None (4)

6 ADVERSE REACTIONS

No adverse reactions were reported in clinical trials with XURIDEN in patients with hereditary orotic aciduria. (6.1)

To report SUSPECTED ADVERSE REACTIONS, contact BTG International Inc. at (1-877-377-3784) or FDA at 1-800-FDA-1088 or www.fda.gov/medwatch.

FULL PRESCRIBING INFORMATION

1 INDICATIONS AND USAGE

XURIDEN®is indicated in adult and pediatric patients for the treatment of hereditary orotic aciduria.

2 DOSAGE AND ADMINISTRATION

2.1 Recommended Dosage

The recommended starting dosage of oral XURIDEN is 60 mg/kg once daily. Increase the dosage of XURIDEN to 120 mg/kg (not to exceed 8 grams) once daily for insufficient efficacy, such as occurrence of one of the following:

- Levels of orotic acid in urine remain above normal or increase above the usual or expected range for the patient
- Laboratory values (e.g., red blood cell or white blood cell indices) affected by hereditary orotic aciduria show evidence of worsening
- Worsening of other signs or symptoms of the disease

The XURIDEN dose to be administered at the 60 mg/kg and 120 mg/kg dose levels by body-weight is presented in Tables 1 and 2.

A 2 gram packet of XURIDEN contains approximately ¾ teaspoon of XURIDEN. Therefore, in the tables below for patients requiring doses in multiples of 2 grams (¾ teaspoon) an entire packet(s) may be administered without weighing or measuring.

XURIDEN Daily Dose Based on Body Weight (kg)

Patient Weight | Table 1: XURIDEN 60 mg/kg [total daily dose by weight category in the tables was rounded to achieve the approximate dose level] Dose Level
Kilograms | Dose to be Administered Using a Scale (grams) | Dose in Teaspoons
up to 5 | 0.4 | ⅛
6-10 | 0.4 to 0.6 | ¼
11-15 | 0.7 to 0.9 | ½
16-20 | 1 to 1.2 | ½
21-25 | 1.3 to 1.5 | ½
26-30 | 1.6 to 1.8 | ¾
31-35 | 1.9 to 2.1 [may use 1 entire 2 gram packet without weighing or measuring] | ¾
36-40 | 2.2 to 2.4 | 1
41-45 | 2.5 to 2.7 | 1
46-50 | 2.8 to 3 | 1
51-55 | 3.1 to 3.3 | 1 ¼
56-60 | 3.4 to 3.6 | 1 ¼
61-65 | 3.7 to 3.9 [may use 2 entire 2 gram packets without weighing or measuring] | 1 ½
66-70 | 4 to 4.2 | 1 ½
71-75 | 4.3 to 4.5 | 1 ½
Above 75 | 6 [may use 3 entire 2 gram packets without weighing or measuring] | 2

Patient Weight | Table 2: XURIDEN 120 mg/kg [total daily dose by weight category in the tables was rounded to achieve the approximate dose level] Dose Level
Kilograms | Dose to be Administered Using a Scale (grams) | Dose in Teaspoons
up to 5 | 0.8 | ¼
6-10 | 0.8 to 1.2 | ½
11-15 | 1.4 to 1.8 | ¾
16-20 | 2 to 2.4 | 1
21-25 | 2.6 to 3 | 1
26-30 | 3.2 to 3.6 | 1 ¼
31-35 | 3.8 to 4.2 [may use 2 entire 2 gram packets without weighing or measuring] | 1 ½
36-40 | 4.4 to 4.8 | 1 ¾
41-45 | 5 to 5.4 | 2 [may use 3 entire 2 gram packets without weighing or measuring]
46-50 | 5.6 to 6 | 2 [may use 3 entire 2 gram packets without weighing or measuring]
51-55 | 6.2 to 6.6 | 2 ¼
56-60 | 6.8 to 7.2 | 2 ½
61-65 | 7.4 to 7.8 | 2 ½
66-70 | 8 | 2 ¾ [may use 4 entire 2 gram packets without weighing or measuring]
71-75 | 8 | 2 ¾ [may use 4 entire 2 gram packets without weighing or measuring]
Above 75 | 8 | 2 ¾ [may use 4 entire 2 gram packets without weighing or measuring]

2.2 Preparation and Administration

Preparation

Measure the dose using either a scale accurate to at least 0.1 gram, or a graduated teaspoon, accurate to the fraction of the dose to be administered.

Once the measured dose has been removed from the XURIDEN packet, discard the unused portion of granules. Do not use any granules left in the open packet.

Administration with Food

1. Place 3 to 4 ounces of applesauce, pudding or yogurt in a small clean container.
2. Mix the measured amount of granules in the applesauce, pudding or yogurt
3. Swallow applesauce/pudding/yogurt immediately. Do not chew the granules. Do not save the applesauce/pudding/yogurt for later use.
4. Drink at least 4 ounces of water.

Administration in Milk or Infant Formula

XURIDEN can be mixed with milk or infant formula instead of the soft foods described above for patients receiving up to 3/4 teaspoon (2 grams) of XURIDEN. After weighing the dose of XURIDEN:

1. Pour 5 mL of milk or infant formula into a 30 mL medicine cup.
2. Insert the tip of the oral syringe into the medicine cup and draw up 5 mL of milk/infant formula into the syringe.
3. Hold the syringe with the tip pointing upward. Pull down on the plunger until the plunger reaches 10 mL. This will add air to the syringe.
4. Place the cap over the tip of the syringe. Then invert the syringe so the syringe tip is pointing down, and remove the plunger.
5. Pour the measured amount of XURIDEN granules into the syringe barrel and reinsert the syringe plunger. Do not push up on the plunger.
6. Gently swirl the syringe to mix the XURIDEN granules with the liquid.
7. Turn the syringe so the syringe tip is pointing up. Then remove the syringe cap and push up on the plunger until the plunger reaches the 5 mL mark. This will remove air from the syringe.
8. Place the tip of the syringe in the patient's mouth between the cheek and gum at the back of the mouth. Gently push the plunger all the way down.
9. Refill the syringe with another 5 mL of milk/infant formula.
10. Gently swirl the syringe to rinse any remaining XURIDEN granules from the syringe barrel.
11. Place the tip of the syringe in the patient's mouth between the cheek and gum at the back of the mouth. Gently push the plunger all the way down.
12. Follow with a bottle of milk or infant formula, if desired.

3 DOSAGE FORMS AND STRENGTHS

Oral granules: 2 grams of orange-flavored oral granules (95% w/w) in single-use packets

4 CONTRAINDICATIONS

None

5 WARNINGS AND PRECAUTIONS

None

6 ADVERSE REACTIONS

6.1 Clinical Trials Experience

Because clinical trials are conducted under widely varying conditions and using a wide range of doses, adverse reaction rates observed in the clinical trials of a drug cannot be directly compared to rates in the clinical trials of another drug and may not reflect the rates observed in practice.

The safety of XURIDEN was assessed in 4 patients with hereditary orotic aciduria ranging in age from 3 to 19 years (3 male, 1 female) who received 60 mg/kg of XURIDEN once daily for six weeks. All patients continued to receive XURIDEN for at least 24 months at dosages of up to 120 mg/kg once daily. No adverse reactions were reported with XURIDEN.

8 USE IN SPECIFIC POPULATIONS

8.1 Pregnancy

Risk Summary

There are no available data on XURIDEN use in pregnant women to inform a drug-associated risk. When administered orally to pregnant rats during the period of organogenesis, uridine triacetate at doses similar to the maximum recommended human dose (MRHD) of 120 mg/kg per day was not teratogenic and did not produce adverse effects on embryo-fetal development [see Data] .

The background risk of major birth defects and miscarriage for the indicated population are unknown. In the U.S. general population, the estimated background risk of major birth defects and miscarriage in clinically recognized pregnancies is 2 to 4% and 15 to 20%, respectively.

Data

Animal Data

In an embryo-fetal development study, uridine triacetate was administered orally to pregnant rats during the period of organogenesis at doses up to 2000 mg/kg per day (about 2.7 times the maximum recommended human dose (MRHD) of 120 mg/kg per day on a body surface area basis). There was no evidence of teratogenicity or harm to the fetus and no effect on maternal body weight and overall health.

8.2 Lactation

Risk Summary

There are no data on the presence of uridine triacetate in human milk, the effect on the breastfed infant or the effect on milk production. The development and health benefits of breastfeeding should be considered along with the mother's clinical need for XURIDEN and any potential adverse effects on the breastfed infant from XURIDEN or from the underlying maternal condition.

8.4 Pediatric Use

The safety and effectiveness of XURIDEN have been established in pediatric patients. Use of XURIDEN is supported by a single open-label clinical trial of uridine triacetate in 4 patients and a retrospective review of the clinical course of 18 patients with hereditary orotic aciduria who were treated with uridine beginning at ages 2 months to 12 years. There are no apparent differences in clinical response between adults and pediatric patients with hereditary orotic aciduria treated with uridine, however, data are limited [see Clinical Studies (14)] .

8.5 Geriatric Use

Clinical trials of XURIDEN did not include patients 65 years of age and older.

11 DESCRIPTION

XURIDEN (uridine triacetate) oral granules is a pyrimidine analog indicated for uridine replacement therapy. Uridine triacetate has the chemical designation (2',3',5'-tri-O-acetyl-β-D-ribofuranosyl)-2,4(1H,3H)-pyrimidinedione. The molecular weight is 370.3 and it has an empirical formula of C15H18N2O9. The structural formula is:

Each single-use 2-gram packet of XURIDEN orange-flavored oral granules (95% w/w) contains 2 grams of uridine triacetate and the following inactive ingredients: ethylcellulose (0.062 grams), Opadry Clear [proprietary dispersion of hydroxypropylmethylcellulose and Macrogol] (0.015 grams), and natural orange juice flavor (0.026 grams).

12 CLINICAL PHARMACOLOGY

12.1 Mechanism of Action

Uridine triacetate is an acetylated form of uridine. Following oral administration, uridine triacetate is deacetylated by nonspecific esterases present throughout the body, yielding uridine in the circulation (Figure 1).

Figure 1: Uridine Triacetate Conversion to Uridine

XURIDEN provides uridine in the systemic circulation of patients with hereditary orotic aciduria who cannot synthesize adequate quantities of uridine due to a genetic defect in uridine nucleotide synthesis.

12.2 Pharmacodynamics

Hereditary orotic aciduria (uridine monophosphate synthase deficiency) is a rare congenital autosomal recessive disorder of pyrimidine metabolism caused by a defect in uridine monophosphate synthase (UMPS). The UMPS gene encodes uridine 5′monophosphate synthase, a bifunctional enzyme that catalyzes the final two steps of the de novo pyrimidine biosynthetic pathway in mammalian cells.

The defect in UMP synthase in hereditary orotic aciduria has two primary biochemical consequences. First, the blockade of de novo UMP synthesis results in a systemic deficiency of pyrimidine nucleotides, accounting for most clinical consequences of the disease. Second, orotic acid from the de novo pyrimidine pathway that cannot be converted to UMP is excreted in the urine, accounting for the common name of the disorder, orotic aciduria. Orotic acid crystals in the urine can cause episodes of obstructive uropathy.

XURIDEN delivers uridine into the circulation, where it can be used by essentially all cells to make uridine nucleotides, compensating for the genetic deficiency in synthesis in patients with hereditary orotic aciduria. When intracellular uridine nucleotides are restored into the normal range, overproduction of orotic acid is reduced by feedback inhibition, so that urinary excretion of orotic acid is also reduced.

12.3 Pharmacokinetics

Absorption

XURIDEN delivers 4- to 6-fold more uridine into the systemic circulation compared to equimolar doses of uridine itself. Maximum concentrations of uridine in plasma following oral XURIDEN are generally achieved within 2 to 3 hours, and the half-life ranges from approximately 2 to 2.5 hours.

A study in patients with hereditary orotic aciduria included an assessment of plasma uridine pharmacokinetics in 4 patients. Three of the patients were previously treated with oral uridine. On Day 0 (baseline), these three patients received their usual daily dose of oral uridine as a single dose (150 to 200 mg/kg once daily) and on Day 1, initiated oral XURIDEN treatment (60 mg/kg once daily). A fourth patient was enrolled who was naïve to uridine replacement therapy. The dose of XURIDEN was increased on Day 116 to 120 mg/kg once daily in two patients (Patients 3 and 4) and plasma uridine concentrations were assessed on Day 160 (44 days after the dose increase).

Plasma uridine levels in all four patients are depicted in Figure 2. Pharmacokinetic parameters are summarized in Table 3. Mean exposure to plasma uridine as assessed by Cmaxand AUC was greater after oral XURIDEN than after oral uridine (approximately 4-fold on an equiweight basis, and 6-fold on an equimolar basis), although individual differences in relative bioavailability were noted. Plasma concentrations of the uridine catabolite uracil were generally below the limit of quantitation in all patients.

Table 3: Pharmacokinetic Parameters for Plasma Uridine
Pharmacokinetic Parameters (Plasma Uridine) | Day 0 (Baseline) (Oral Uridine, 150 to 200 mg/kg once daily) N = 3 [Data shown are from patients previously treated with oral uridine] | Day 1 (Oral XURIDEN, 60 mg/kg once daily) N = 4 | Day 28 (Oral XURIDEN, 60 mg/kg once daily) N = 4 | Day 160 (Oral XURIDEN, 120 mg/kg once daily) N = 2 [The dose of XURIDEN was increased on Day 116 to 120 mg/kg per day. Serial plasma samples were taken on Day 160 (44 days after the dose increase) for plasma uridine levels.]
Cmax(µM) mean ± SD | 56.0 ± 16.6 | 91.3 ± 32.2 | 88.7 ± 43.2 | 80.9 ± 20.0
Tmax(hours) median (range [T max range is expressed as the minimum and maximum values obtained]) | 2.0 (1.0, 4.0) | 2.0 (1.2, 2.1) | 1.3 (1.0, 2.5) | 3.0 (2.0, 4.0)
t½(hours) mean ± SD | 1.6 ± 0.7 | 1.6 ± 0.6 | 2.3 ± 1.6 | 8.2 ± 6.8
AUC(0-8)(µM∙hr) mean ± SD | 238.0 ± 163.2 | 311.2 ± 153.3 | 278.7 ± 148.5 | 465.6 ± 95.3

Figure 2 Plasma Uridine Following Oral Administration of Uridine (Day 0) or XURIDEN (Days 1, 28 and 160) in Patients with Hereditary Orotic Aciduria

Food Effect on Uridine PK:A study in healthy adult subjects receiving a slightly different formulation of uridine triacetate granules (6 gram dose) under fed and fasted conditions showed no difference in the overall rate and extent of uridine exposure.

Distribution

Circulating uridine is taken up into mammalian cells via specific nucleoside transporters, and also crosses the blood brain barrier.

Excretion

Uridine can be excreted via the kidneys, but is also metabolized by normal pyrimidine catabolic pathways present in most tissues.

Drug Interaction Studies

In vitroenzyme inhibition data did not reveal meaningful inhibitory effects of uridine triacetate or uridine on CYP3A4, CYP1A2, CYP2C8, CYP2C9, CYP2C19, CYP2D6, and CYP2E1. In vitroenzyme induction data did not reveal an inducing effect of uridine triacetate or uridine on CYP1A2, CYP2B6, or CYP3A4.

In vitrodata showed that uridine triacetate was a weak substrate for P-glycoprotein. Uridine triacetate inhibited the transport of a known P-glycoprotein substrate, digoxin, with an IC50 of 344 µM. Due to the potential for high local (gut) concentrations of the drug after dosing, the interaction of XURIDEN with orally administered P-gp substrate drugs cannot be ruled out.

In vivodata in humans are not available.

13 NONCLINICAL TOXICOLOGY

13.1 Carcinogenesis, Mutagenesis, Impairment of Fertility

Long-term studies in animals have not been performed to evaluate the carcinogenic potential of uridine triacetate.

Uridine triacetate was not genotoxic in the Ames test, the mouse lymphoma assay and the mouse micronucleus test.

Orally administered uridine triacetate did not affect fertility or general reproductive performance in male and female rats at doses up to 2000 mg/kg per day (about 2.7 times the maximum recommended human dose (MRHD) of 120 mg/kg per day on a body surface area basis).

14 CLINICAL STUDIES

The efficacy of XURIDEN was evaluated in a 6-week open-label study in 4 patients with hereditary orotic aciduria (3 male, 1 female; age range from 3 to 19 years). Three patients were previously treated with uridine and were switched at study entry to XURIDEN. All patients were administered XURIDEN orally at a daily dosage of 60 mg/kg once daily. Following the initial 6-weeks, all 4 patients continued to receive XURIDEN daily in the extension phase of the study at dosages of 60 to 120 mg/kg for a total duration of 24 months.

The study assessed changes in the patients' pre-specified hematologic parameters during the initial 6-week period and the extension phase. The pre-specified hematologic parameters were: neutrophil count and percent neutrophils (Patient 1), white blood cell count (Patient 2), and mean corpuscular volume (Patients 3 and 4). For patients switched from oral uridine to oral XURIDEN (Patients 1, 2, and 3), the primary endpoint was stability of the hematologic parameter; for the treatment-naïve patient (Patient 4), the primary endpoint was improvement of the hematologic parameter.

Secondary endpoints were urine orotic acid and orotidine levels, and growth (height and weight) for all patients.

Table 4 summarizes the changes in the patients' pre-specified hematologic parameters at Week 6 and 24 Months compared to baseline. After 6 weeks of treatment, Patients 1 and 3 met the pre-specified criteria for stability of the hematologic parameter. When Patient 2 was switched from uridine to XURIDEN treatment, the pre-specified parameter of white blood cell count remained stable; however, documentation of a low white blood cell count prior to uridine initiation was not available. Patient 4 did not meet the pre-specified endpoint of improvement of the hematologic parameter.

By 24 months of treatment with XURIDEN, the pre-specified hematologic parameter for Patient 1 worsened, but the assessment was confounded by Cohen syndrome with associated neutropenia, which was diagnosed after the patient completed the study. The pre-specified hematologic parameters for Patients 2, 3, and 4 remained essentially unchanged.

Table 4: Pre-Specified Hematologic Parameters at Baseline, 6 Weeks and 24 Months in XURIDEN-Treated Patients with Hereditary Orotic Aciduria
Patient | Pre-specified Hematologic Parameter (Age-specific reference range) | Baseline (Day 0) | 6 Weeks (% Change from Baseline) | 24 Months (% Change from Baseline)
Patient 1 | Neutrophil Count (1.5 to 8.0 x10^3/mm^3) | 0.95 | 0.81 (-15%) | 0.61 (-36%)
Patient 1 | Neutrophil % (26 to 48%) | 21 | 23 (10%) | 13 (-38%)
Patient 2 | White Blood Cell Count (3.8 to 10.6 x10^9/L) | 7.8 | 7.4 (-5%) | 8.6 (10%)
Patient 3 | Mean Corpuscular Volume (75 to 91 fL) | 109.9 | 108.5 (-1%) | 108.8 (-1%)
Patient 4 | Mean Corpuscular Volume (72 to 90 fL) | 114.6 | 113.4 (-1%) | 112.9 (-1.5%)

At baseline, Patients 1, 2, and 3, previously treated with uridine, had normal urine orotic acid levels, and those remained stable after 6 weeks of treatment with XURIDEN. All four patients had normal urine orotidine levels at baseline which remained stable after 6 weeks of treatment with XURIDEN. After 24 months of treatment, urine orotic acid and orotidine levels remained stable in all four patients.

The treatment effect of XURIDEN on growth was assessed in the three pediatric patients (Patients 1, 3, and 4). At baseline, weight and height were at or below the lower limit of normal for age for all three patients. After 24 months of treatment, each patient's growth parameters remained essentially unchanged.

Case reports

Nineteen (19) case reports of patients with hereditary orotic aciduria have been documented in published literature. Eighteen (18) patients were diagnosed as infants or children between the ages of 2 months and 12 years and were treated with exogenous sources of uridine. One patient, diagnosed at age 28, was not treated with exogenous uridine.

All 19 patients presented with significantly elevated levels of urinary orotic acid. Fifteen of 19 had abnormal hematologic parameters at presentation, including 15 with megaloblastic anemia, 8 with leukopenia and at least 2 with neutropenia. Oral administration of exogenous sources of uridine was reported to significantly improve hematologic abnormalities (megaloblastic anemia, leukopenia and neutropenia) within 2 to 3 weeks in almost all documented cases when administered in sufficient amounts. Concentrations of urinary orotic acid were significantly reduced within 1 to 2 weeks of initiating uridine replacement therapy. Some fluctuation in levels of urinary orotic acid were observed, but always at much lower levels than those reported prior to treatment. Improvements in body weight were also documented over time with continued uridine replacement therapy.

The effects of exogenous uridine were maintained over months and years, as long as treatment continued at sufficient doses (with appropriate dose increases based on body weight increases). Most hematologic abnormalities and orotic aciduria reappeared within days up to 2 or 3 weeks when administration of uridine was stopped or the dose was reduced. If treatment was interrupted for longer periods, body weight growth receded. If absolute dosages were not adjusted adequately to compensate for body weight gains, signs and symptoms of hereditary orotic aciduria recurred.

16 HOW SUPPLIED/STORAGE AND HANDLING

XURIDEN orange-flavored oral granules (95% w/w) are available in single-use packets (NDC 50633-330-02) containing 2 grams of uridine triacetate in cartons of 30 packets each (NDC 50633-330-30).

STORAGE AND HANDLING

Store at controlled room temperature, 25°C (77°F); excursions permitted to 15° to 30°C (59° to 86°F).

17 PATIENT COUNSELING INFORMATION

Advise the patient or caregiver to read the FDA-approved patient labeling (Instructions for Use)

Administration

Advise the patient or caregiver:

- To measure the prescribed dose using either a scale accurate to at least 0.1 gram, or a graduated teaspoon, accurate to the fraction of the dose to be administered.
- To discard the unused portion of granules in a packet after measuring out the dose.
- That XURIDEN can be taken mixed in food (applesauce, pudding or yogurt) or mixed in milk or infant formula.
- That the XURIDEN granules should not be chewed.

Manufactured for and distributed by: -

BTG International Inc.
West Conshohocken, PA, 19428

XURIDEN®is a registered trademark of BTG International Inc. The SERB logo is a registered trademark of SERB S.à.r.l.

Instructions for Use XURIDEN®(ZUR-uh-den) (uridine triacetate) oral granules

Read this Instructions for Use before you prepare XURIDEN for the first time, each time you get a refill, and as needed. There may be new information. This information does not take the place of talking to your healthcare provider about your or your child's medical condition or treatment. Ask your healthcare provider if you have any questions about how to mix or give a dose of XURIDEN the right way.

Important Information

- Take XURIDEN exactly as your healthcare provider tells you to.
- Your healthcare provider will prescribe the dose of XURIDEN depending on your body weight. Your healthcare provider will tell you the right dose to take.
- Your healthcare provider will show you how to measure the prescribed dose. The prescribed dose of XURIDEN can be measured using a scale or an adjustable measuring spoon.
- Your healthcare provider may change your dose if needed. Do not change the dose without first talking with your healthcare provider.
- XURIDEN may be taken by mixing XURIDEN with 3 to 4 ounces of applesauce, pudding or yogurt or may be mixed with milk or infant formula.
- XURIDEN mixed with applesauce, pudding or yogurt should be eaten right away. Do not save the mixed applesauce, pudding or yogurt for later use.
- Do notchew the XURIDEN oral granules.

For each dose of XURIDEN given in applesauce, pudding or yogurt, you will need the following (See Figure A):

- paper towels
- XURIDEN packet or packets containing the medicine needed for the prescribed dose
- 1 scale or 1 adjustable measuring spoon
- small spoon for stirring
- 1 small clean container (such as a small cup or bowl)
- 3 to 4 ounces of applesauce, pudding or yogurt
- 4 ounces of drinking water

Figure A

Step 1: | Choose a clean flat work surface. Place a clean paper towel on the work surface. Then place the other supplies on the paper towel.
Step 2: | Wash and dry your hands.
Step 3: | Place 3 to 4 ounces of soft food such as applesauce, pudding, or yogurt in the small clean cup or bowl.
Step 4: | Select the number of XURIDEN packets needed for the prescribed dose.
Step 5: | Measure the dose:
- If you are using a scale: - Open the packet or packets and measure out the amount needed for the prescribed dose on the scale. Follow the instructions that came with the scale for correct and accurate use. - If you are using an adjustable measuring spoon: - Open the packet or packets and use the adjustable measuring spoon to measure out the amount needed for the prescribed dose as shown. - Throw away any unused XURIDEN in the trash. Do not use any XURIDEN left in the open packet.
Step 6: | Sprinkle the XURIDEN onto the soft food.
Step 7: | Use the small spoon to mix the medicine and the applesauce, pudding, or yogurt together.
Step 8: | Use the small spoon to give or take the soft food and XURIDEN mixture. XURIDEN mixed with soft food should be eaten right away without chewing.To avoid a bitter taste from the medicine, do not chew the granules. Make sure all of the mixture is swallowed. Do notsave the food for later use.
Step 9: | Drink at least 4 ounces of water.
Step 10: | Wash the supplies needed to give the dose as your healthcare provider has told you. Throw away the paper towel and clean the work surface. Wash your hands.

For each dose of XURIDEN given in milk or formula to children receiving up to ¾ teaspoon (2 grams of XURIDEN), you will need the following (See Figure B):

- paper towels
- XURIDEN packet or packets containing the medicine needed for your prescribed dose
- 1 oral dosing syringe (10mL) with a cap
- 1 scale or 1 adjustable measuring spoon
- milk or infant formula (10mL)
- 1 medicine cup (30mL)

Figure B

Step 1: | Choose a clean flat work surface. Place a clean paper towel on the work surface. Then place the other supplies on the paper towel.
- If using infant formula, prepare the formula according to the directions on the infant formula package.
Step 2: | Wash and dry your hands.
Step 3: | Open one XURIDEN packet.
Step 4: | Measure the dose:
- If you are using a scale: - Open the packet and measure out the amount needed for the prescribed dose on the scale. Follow the instructions that came with the scale for correct and accurate use. - If you are using an adjustable measuring spoon: - Open the packet and use the adjustable measuring spoon to measure out the amount needed for the prescribed dose as shown. - Throw away any unused XURIDEN in the trash. Do not use any XURIDEN left in the open packet.
Step 5: | Pour 5 mL of either milk or infant formula into the 30mL medicine cup.
Step 6: | Place the syringe tip into the medicine cup. Pull up on the plunger until all the liquid is removed from the cup and the plunger reaches the 5 mL line on the syringe.
Step 7: | Hold the syringe with the tip pointing upward. Pull down on the plunger until the plunger reaches the 10 mL line on the syringe. This will add air to the syringe.
Step 8: | Place the syringe cap over the tip of the syringe. Now hold the syringe so the tip is pointing down and remove the plunger.
Step 9: | Pour the measured amount of XURIDEN granules into the syringe barrel, and put the plunger back in. Do not push further on the plunger.
Step 10: | Gently swirl the syringe to mix the XURIDEN with the liquid.
Step 11: | Turn the syringe so the syringe tip is pointing up, then remove the syringe cap, and push up on the plunger until the plunger reaches the 5mL line on the syringe. This will remove the air from the syringe.
Step 12: | Give the mixture to the child right awayto avoid a bitter taste from the medicine. Place the tip of the syringe in your child's mouth between the cheek and the gum at the back of the mouth. Gently push the plunger all the way down.
Step 13: | Pour another 5 mL of milk or formula into the medicine cup.
Step 14: | Refill the syringe by placing the syringe tip into the medicine cup. Pull up on the plunger until all the liquid is removed from the cup and the plunger reaches the 5 mL line on the syringe.
Step 15: | Gently swirl the syringe to make sure any medicine remaining in the syringe is mixed with the liquid.
Step 16: | Give the liquid to the child right away. Place the tip of the syringe in your child's mouth between the cheek and the gum at the back of the mouth. Gently push the plunger all the way down.
Step 17: | Give your child a bottle of milk or formula after giving the XURIDEN dose if you wish to.
Step 18: | Remove the plunger from the barrel of the dosing syringe and wash the syringe and mixing cup, with warm water and dish soap. Rinse with water and air dry.
- Wash the supplies needed to measure your dose as your healthcare provider has told you. - Throw away the paper towel and clean the work surface. - Wash your hands.

How should I store XURIDEN?

- Store XURIDEN at room temperature between 59° F to 86°F (15° to 30°C).
- Keep XURIDEN and all medicines out of the reach of children.

General information about the safe and effective use of XURIDEN

This Instructions for Use leaflet summarizes the most important information about XURIDEN. If you would like more information, talk with your healthcare provider. You can ask your healthcare provider or pharmacist for information about XURIDEN that is written for healthcare professionals.

For more information, go to www.XURIDEN.com.

What are the ingredients in XURIDEN?

Active ingredient:uridine triacetate

Inactive ingredients:ethylcellulose, hydroxypropylmethylcellulose, Macrogol, natural orange juice flavor

This Instructions for Use has been approved by the U.S. Food and Drug Administration.

Manufactured for and distributed by
BTG International Inc,
West Conshohocken, PA, 19428

XURIDEN®is a registered trademark of BTG International Inc.

Issued: 08/2023

PRINCIPAL DISPLAY PANEL - 2 g Packet Label

NDC 50633-330-02
RxOnly

Xuriden®2 g
(uridine triacetate)

Oral Granules

Packet contains 1 x 2 gram packets

BTG International Inc

PRINCIPAL DISPLAY PANEL - 30 Count Carton Label

NDC 50633-330-30
RxOnly

Xuriden®2 g
(uridine triacetate)

Oral Granules

Carton contains 30 x 2 gram packets

BTG International Inc